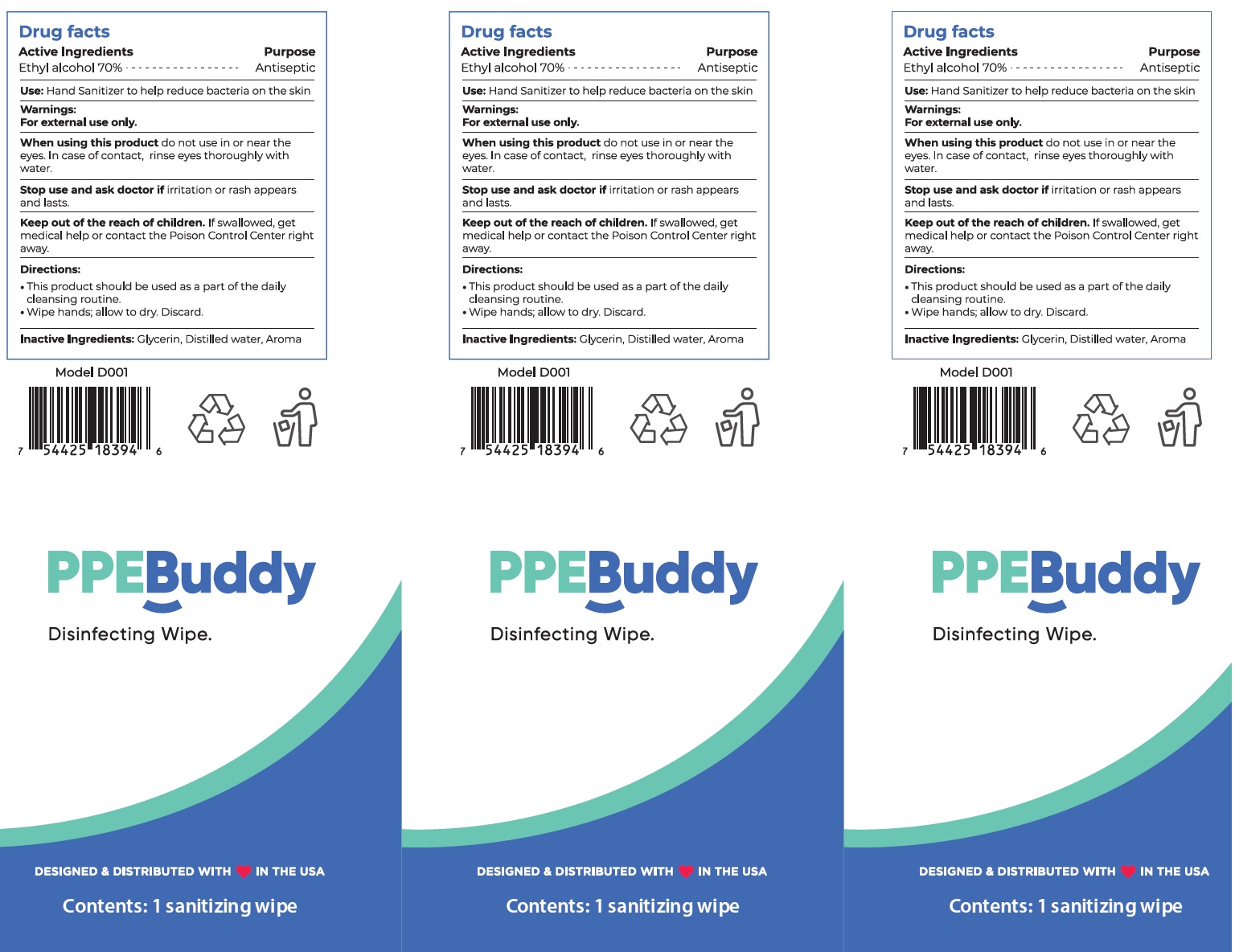 DRUG LABEL: PPEBuddy Disinfecting Wipe D001
NDC: 79437-003 | Form: CLOTH
Manufacturer: PPE Buddy LLC
Category: otc | Type: HUMAN OTC DRUG LABEL
Date: 20200806

ACTIVE INGREDIENTS: ALCOHOL 0.7 mL/1 mL
INACTIVE INGREDIENTS: GLYCERIN; WATER

PPEBuddy - Disinfecting Wipe

Active Ingredients

Ethyl alcohol 70%

Purpose

Antiseptic

Use

Hand Sanitizer to help reduce bacteria on the skin

Warnings

For external use only.

When using this product

do not use in or near eyes. In case of contact, rinse eyes thoroughly with water.

Stop use and ask a doctor if

irritation or rash appears and lasts.

Keep out of reach of children.

If swallowed, get medical help or contact a Poison Control Center right away.

Directions:

This product should be used as a part of the daily cleansing routine.

Wipe hands; allow to dry. Discard.

Inactive Ingredients:

Glycerin, Distilled water, Aroma